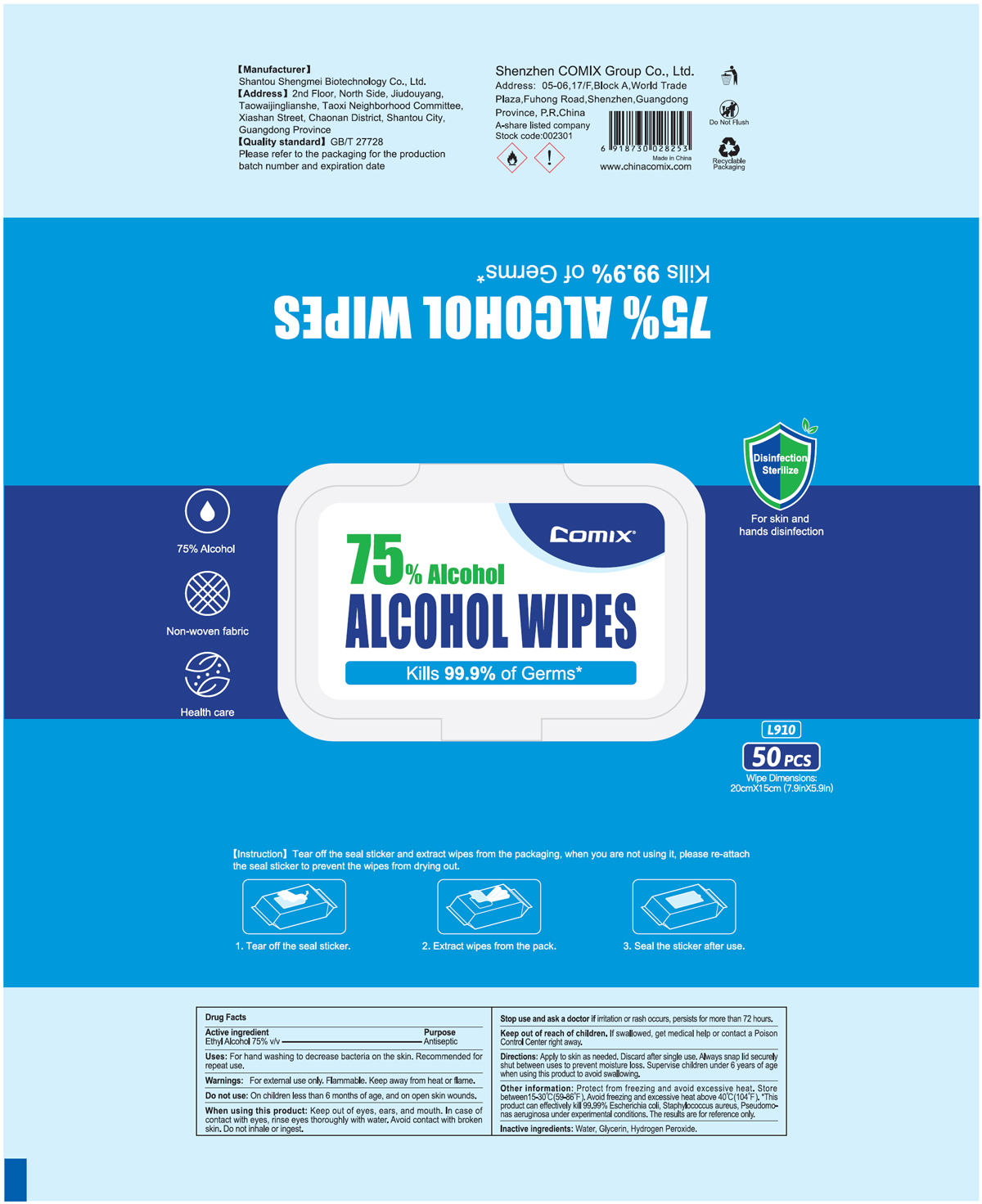 DRUG LABEL: Comix Alcohol Wipes
NDC: 55450-009 | Form: CLOTH
Manufacturer: Shantou Shengmei Biotechnology Co., Ltd.
Category: otc | Type: HUMAN OTC DRUG LABEL
Date: 20200820

ACTIVE INGREDIENTS: ALCOHOL 75 mL/100 g
INACTIVE INGREDIENTS: GLYCERIN; HYDROGEN PEROXIDE; WATER

Comix Alcohol Wipes

Active Ingredient

Ethyl Alcohol 75% v/v. Purpose: Antiseptic

Purpose

Antiseptic, Wipes

Uses

For hand washing to decrease bacteria on the skin. Recommended for repeat use.

Warnings

For external use only. Flammable. Keep away from heat or flame.

Do not use

on children less than 6 months of age, and on open skin wounds.

When using this product

Keep out of eyes, ears, and mouth. In case of contact with eyes, rinse eyes thoroughly with water. Avoid contact with broken skin. Do not inhale or ingest.

Stop use and ask doctor

if irritation or rash occurs, persists for more than 72 hours.

Keep out of reach of children.

If swallowed, get medical help or contact a Poison Control Center right away.

Directions

Apply to skin as needed. Discard after single use. Always snap lid securely shut between uses to prevent moisture loss. Supervise children under 6 years of age when using this product to avoid swallowing.

Other information

Protect from freezing and avoid excessive heat. Store between 15-30C (59-86F). Avoid freezing and excessive heat above 40C (104F). * This product can effectively kills 99.99% Escherichia coli, Staphylococcus aureus, Pseudomonas aeruginosa under experimental conditions. The results are for reference only.

Inactive ingredients

Water, Glycerin, Hydrogen Peroxide

PACKAGE LABEL

55450-009-01 50PCS

Comix

75% ALCOHOL WIPES

Kills 99.99% of Germs*

Disinfection

Sterilize

For skin and hands protection

75% Alcohol

Non-woven fabric

Health care

L910

50 PCS

Wipe Dimensions

20cm X 15cm (7.9in X 5.9in)